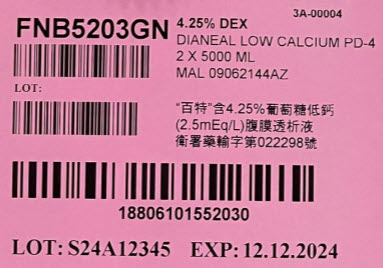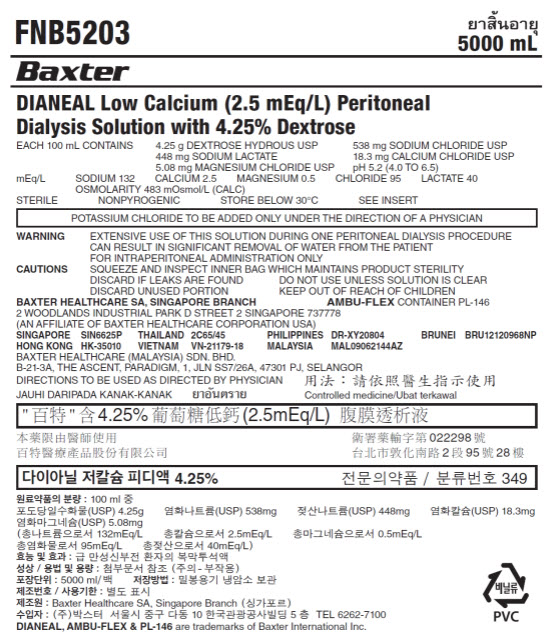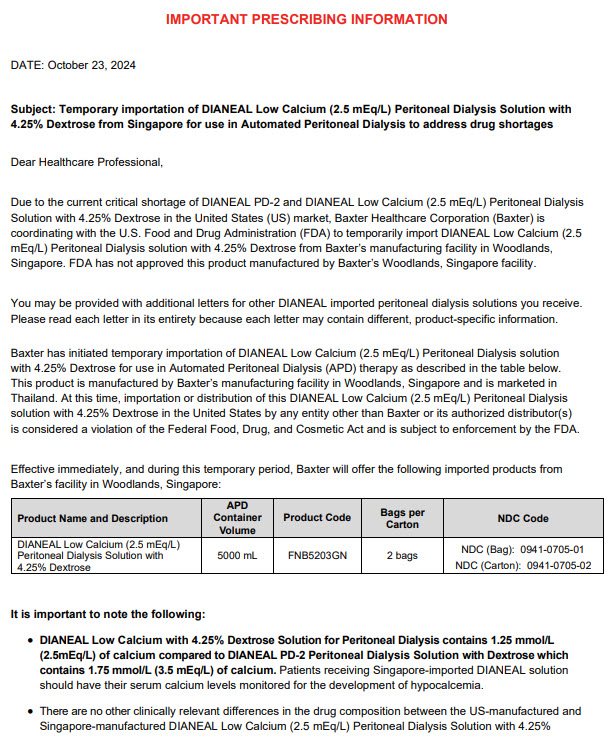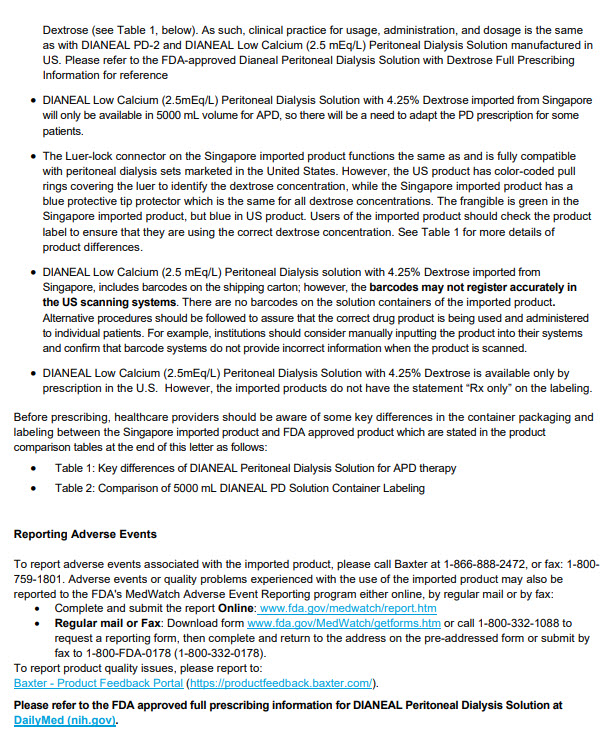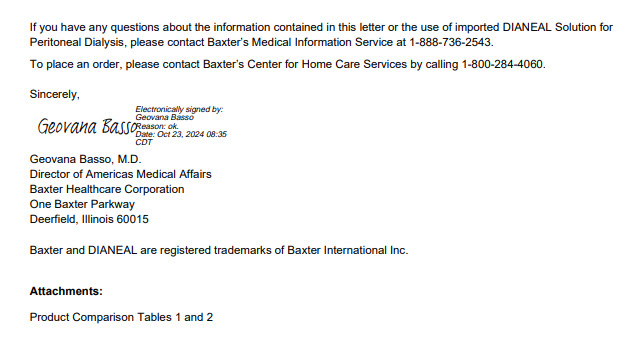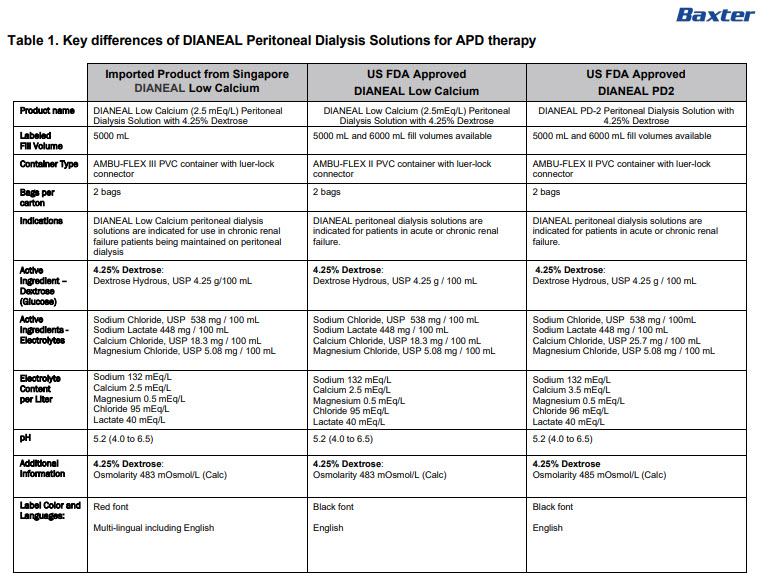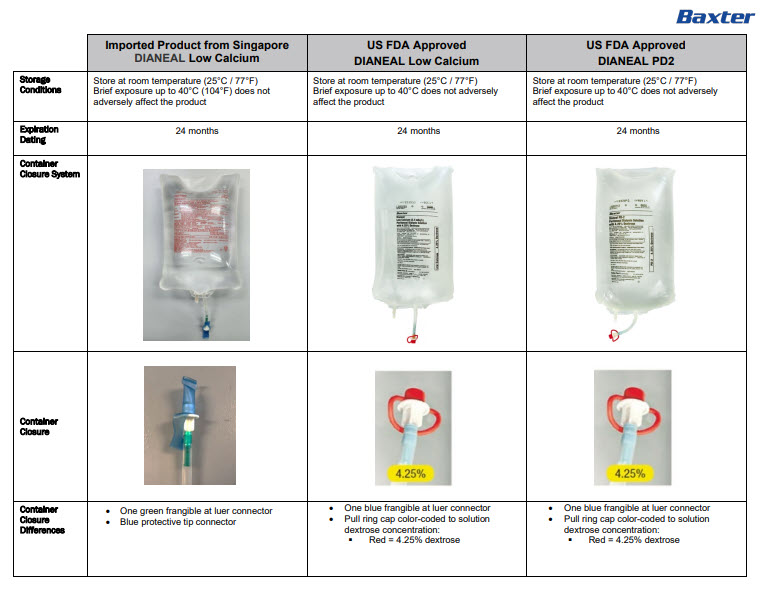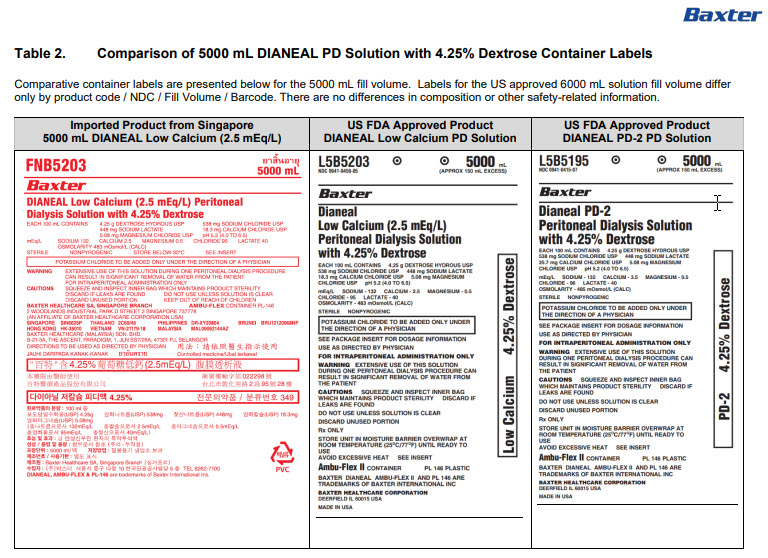 DRUG LABEL: DIANEAL LOW CALCIUM WITH DEXTROSE
NDC: 0941-0705 | Form: INJECTION, SOLUTION
Manufacturer: Vantive US Healthcare LLC
Category: prescription | Type: HUMAN PRESCRIPTION DRUG LABEL
Date: 20250509

ACTIVE INGREDIENTS: DEXTROSE MONOHYDRATE 4.25 g/100 mL; SODIUM CHLORIDE 538 mg/100 mL; SODIUM LACTATE 448 mg/100 mL; CALCIUM CHLORIDE 18.3 mg/100 mL; MAGNESIUM CHLORIDE 5.08 mg/100 mL
INACTIVE INGREDIENTS: WATER

DIANEAL Low Calcium with Dextrose

PACKAGE/LABEL PRINCIPAL DISPLAY PANEL

FNB5203
5000 mL

BaxterLogo

DIANEAL Low Calcium (2.5 mEq/L) Peritoneal
Dialysis Solution with 4.25% Dextrose

EACH 100 mL CONTAINS 4.25 g DEXTROSE HYDROUS USP 538 mg SODIUM CHLORIDE USP
448 mg SODIUM LACTATE 18.3 mg CALCIUM CHLORIDE USP
5.08 mg MAGNESIUM CHLORIDE USP pH 5.2 (4.0 to 6.5)
mEq/L SODIUM 132 CALCIUM 2.5 MAGNESIUM 0.5 CHLORIDE 95 LACTATE 40
OSMOLARITY 483 mOsmol/L (CALC)
STERILE NONPYROGENIC STORE BELOW 30°C SEE INSERT

POTASSIUM CHLORIDE TO BE ADDED ONLY UNDER THE DIRECTION OF A PHYSICIAN

WARNING
EXTENSIVE USE OF THIS SOLUTION DURING ONE PERITONEAL DIALYSIS PROCEDURE
CAN RESULT IN SIGNIFICANT REMOVAL OF WATER FROM THE PATIENT
FOR INTRAPERITONEAL ADMINISTRATION ONLY

CAUTIONS
SQUEEZE AND INSPECT INNER BAG WHICH MAINTAINS PRODUCT STERILITY
DISCARD IF LEAKS ARE FOUND DO NOT USE UNLESS SOLUTION IS CLEAR
DISCARD UNUSED PORTION KEEP OUT OF REACH OF CHILDREN

BAXTER HEALTHCARE SA, SINGAPORE BRANCH AMBU-FLEXCONTAINER PL-146
2 WOODLANDS INDUSTRIAL PARK D STREET 2 SINGAPORE 737778
(AN AFFLIATE OF BAXTER HEALTHCARE CORPORATION USA)
SINGAPORE SIN6625P THAILAND 2C65/45 PHILIPPINES DR-XY20804 BRUNEI BRU12120968NP
HONG KONG HK-35010 VIETNAM VN-21179-18 MALAYSIA MAL09062144AZ
BAXTER HEALTHCARE (MALAYSIA) SDN, BHD.
B-21-3A, THE ASCENT, PARADIGM, 1, JLN SS7/26A,47301 PJ, SELANGOR
DIRECTIONS TO BE USED AS DIRECTED BY PHYSICIAN

JAUHI DARIPADA KANAK-KANAK
Controlled medicine/Ubat terkawal

Baxter Healthcare SA, Singapore Branch
10 5 TEL 6262-7100
DIANEAL, AMBU-FLEX & PL-146are trademarks of Baxter International Inc.

PVCsymbol

3A-00004

FNB5203GN

4.25% DEX
DIANEAL LOW CALCIUM PD-4
2 X 5000 ML
MAL 09062144AZ

Barcode
Lot:
Barcode

4.25%
(2.5mEq/L)
022298

Barcode
18806101552030

LOT: S24A12345 EXP: 12.12.2024